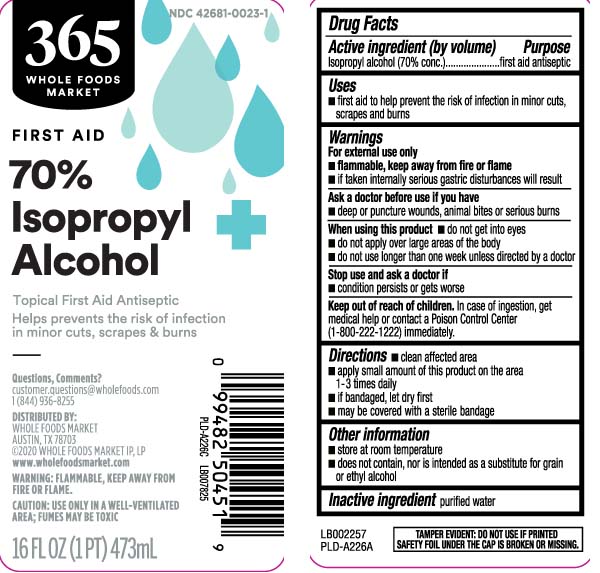 DRUG LABEL: Isopropyl alcohol
NDC: 42681-0023 | Form: LIQUID
Manufacturer: Whole Foods Market
Category: otc | Type: HUMAN OTC DRUG LABEL
Date: 20250307

ACTIVE INGREDIENTS: ISOPROPYL ALCOHOL 70 mL/100 mL
INACTIVE INGREDIENTS: WATER

Drug Facts

Active ingredient (by volume)

Isopropyl alcohol (70% conc.)

Purpose

First aid antiseptic

Uses

- first aid to help prevent the risk of infection in minor cuts, scrapes, and burns.

Warnings

For external use only

- Flammable, keep away from fire or flame
- if taken internally serious gastric disturbances will result

Ask a doctor before use if you have

- deep or puncture wounds, animal bites, or serious burns.

When using this product

- do not get into eyes
- do not apply over large areas of the body
- do not use longer than one week unless directed by a doctor

Stop use and ask a doctor if

- condition persists or gets worse.

Keep out of reach of children.

In case of ingestion, get medical help or contact a Poison Control Center (1-800-222-1222.immediately.

Directions

- clean affected area
- apply small amount of this product on the area 1-3 times daily
- if bandaged, let dry first
- may be covered with a sterile bandage

Other information

- store at room temperature
- does not contain, nor is intended as a substitute for grain or ethyl alcohol

Inactive ingredient

purified water

Principal Display Panel

FIRST AID

70% Isopropyl Alcohol

Topical First Aid Antiseptic

Helps prevents the risk of infection in minor cuts, scrapes & burns

Questions, Comments?

customer, questions @wholefoods.com 1 (844) 936-8255

DISTRIBUTED BY:

WHOLE FOODS MARKET

AUSTIN, TX 78703

www.wholefoodsmarket.com

WARNING: FLAMMABLE, KEEP AWAY FROM FIRE OR FLAME.

CAUTION: USE ONLY IN A WELL-VENTILATED AREA; FUMES MAY BE TOXIC

Package Label

365 WHOLE FOODS MARKET 70% Isopropyl Alcohol